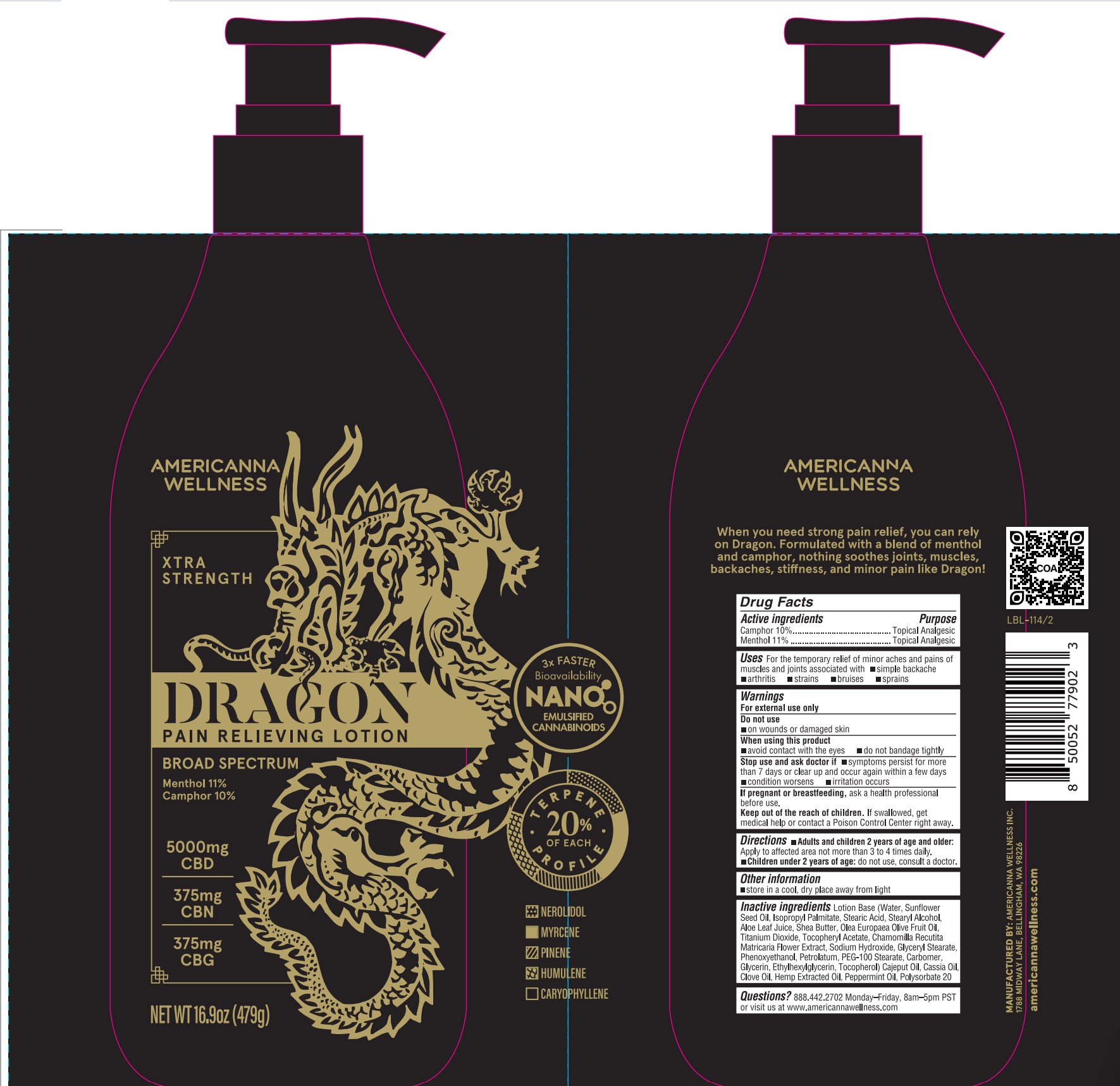 DRUG LABEL: Dragon Pain Relieving
NDC: 83552-120 | Form: LOTION
Manufacturer: AMERICANNA WELLNESS, INC.
Category: otc | Type: HUMAN OTC DRUG LABEL
Date: 20251124

ACTIVE INGREDIENTS: CAMPHOR (SYNTHETIC) 10 g/100 g; MENTHOL 11 g/100 g
INACTIVE INGREDIENTS: CAJUPUT OIL; STEARYL ALCOHOL; PEG-100 STEARATE; PEPPERMINT OIL; SUNFLOWER SEED; SHEA BUTTER; GLYCERYL MONOSTEARATE; ETHYLHEXYLGLYCERIN; TOCOPHEROL; CLOVE OIL; SODIUM HYDROXIDE; CARBOMER HOMOPOLYMER, UNSPECIFIED TYPE; CHINESE CINNAMON OIL; POLYSORBATE 20; PETROLATUM; CANNABIS SATIVA SEED OIL; ISOPROPYL PALMITATE; STEARIC ACID; ALOE VERA LEAF; WATER; OLIVE OIL; TITANIUM DIOXIDE; .ALPHA.-TOCOPHEROL ACETATE; MATRICARIA CHAMOMILLA FLOWERING TOP; PHENOXYETHANOL; GLYCERIN

Dragon Pain Relieving Lotion 16.9oz

Active ingredients

Camphor 10%

Menthol 11%

Purpose

Camphor 10%................Topical Analgesic

Menthol 11%..................Topical Analgesic

Uses

For the temporary relief of minor aches and pains of muscles and joints associated with

- simple backache
- arthritis
- strains
- bruises
- sprains

Warnings

For external use only

Do not use

- on wounds or damaged skin

When using this product

- avoid contact with eyes
- do not bandage tightly

Stop use and ask doctor if

- symptoms perists for more than 7 days or clear up and occur again within a few days
- condition worsens
- irritation occurs

PREGNANCY OR BREAST FEEDING

If pregnant or breastfeeding,ask a health professional before use.

Keep out of reach of children.If swallowed, get medical help or contact a Poison Control Center right away.

Directions

- Adults and children 2 years of age and older:Apply to affected area not more than 3 to 4 times daily.
- Children under 2 years of age:do not use, consult a doctor.

Other information

- store in a cool, dry place away from light

Inactive ingredients

Lotion Base (Water, Sunflower Seed Oil, Isopropyl Palmitate, Stearic Acid, Stearyl Alcohol, Aloe Leaf Juice, Shea Butter, Olea Europaea Olive Fruit Oil, Titanium Dioxide, Tocopheryl Acetate, Chamomilla Recutita Matricaria Flower Extract, Sodium Hydroxide, Glyceryl Stearate, Phenoxyethanol, Petrolatum, PEG-100 Stearate, Carbomer, Glycerin, Ethylhexylglycerin, Tocopherol) Cajeput Oil, Cassia Oil, Clove Oil, Hemp Extracted Oil, Peppermint Oil, Polysorbate 20

Questions?

888.442-2702 Monday-Friday, 8am-5pm PST or visit us at www.americannawellness.com

PACKAGE LABEL

AMERICANNA WELLNESS

XTRA STRENGTH

DRAGON PAIN RELIEVING LOTION

BROAD SPECTRUM

Menthol 11%

Camphor 10%

5000mg CBD

375mg CBN

375mg CBG

NET WT 16.9oz (479g)